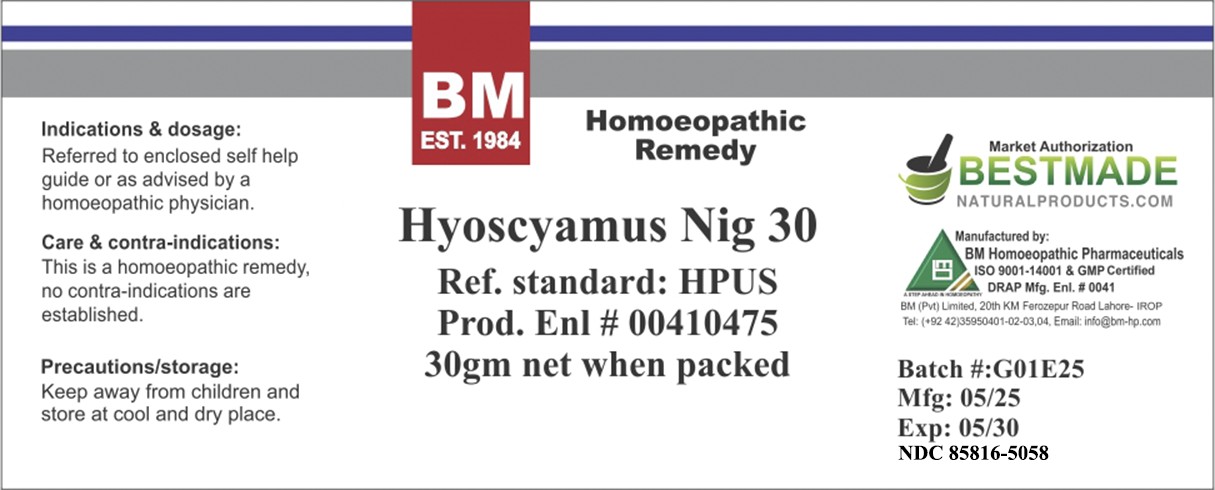 DRUG LABEL: BM Hyoscyamus Niger
NDC: 85816-5058 | Form: GLOBULE
Manufacturer: BM Private Limited
Category: homeopathic | Type: HUMAN OTC DRUG LABEL
Date: 20260217

ACTIVE INGREDIENTS: HYOSCYAMUS NIGER 30 [hp_C]/1000 mg
INACTIVE INGREDIENTS: SUCROSE 1000 mg/1000 mg

BM Hyoscyamus Niger

Indications & dosage:
Referred to enclosed self help guide or as advised by a homoeopathic physician.

INACTIVE INGREDIENT

sucrose

ACTIVE INGREDIENT

Hyoscyamus Niger

Indications & dosage:
Referred to enclosed self help guide or as advised by a homoeopathic physician.

PURPOSE

Indications & dosage:
Referred to enclosed self help guide or as advised by a homoeopathic physician.

CONTRAINDICATIONS

Care & contra-indications:
This is a homoeopathic remedy, no contra-indications are established.

WARNINGS

Precautions/storage:
Keep away from children and store at cool and dry place.

KEEP OUT OF REACH OF CHILDREN

Precautions/storage:
Keep away from children and store at cool and dry place.

Package 1: